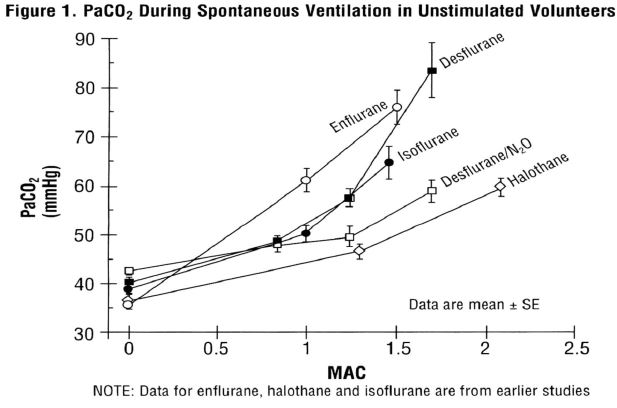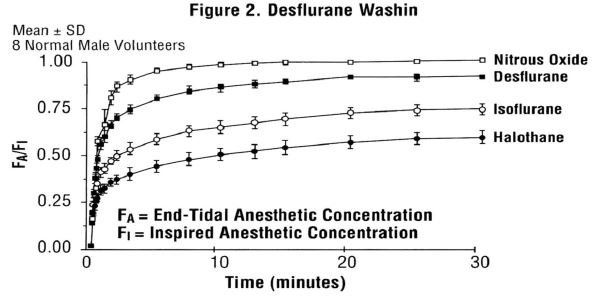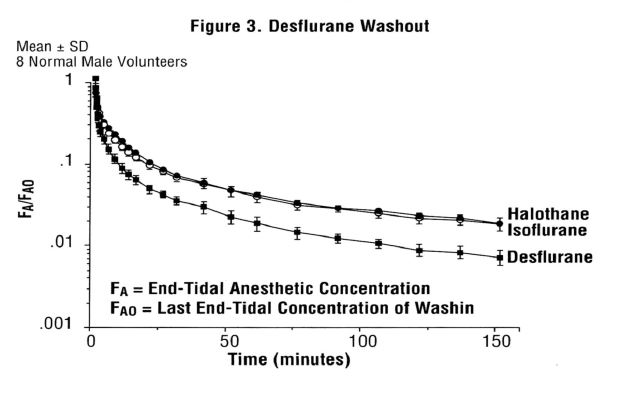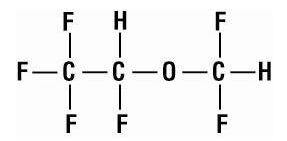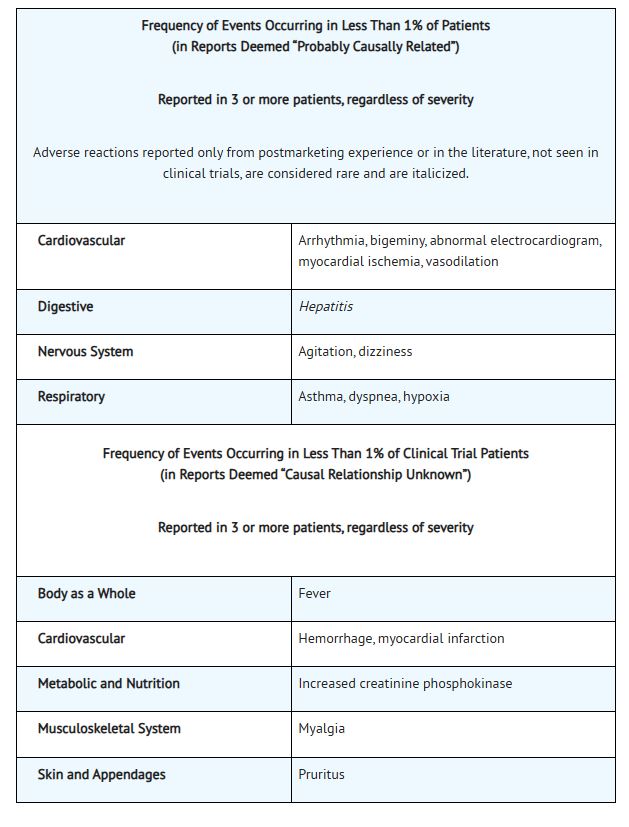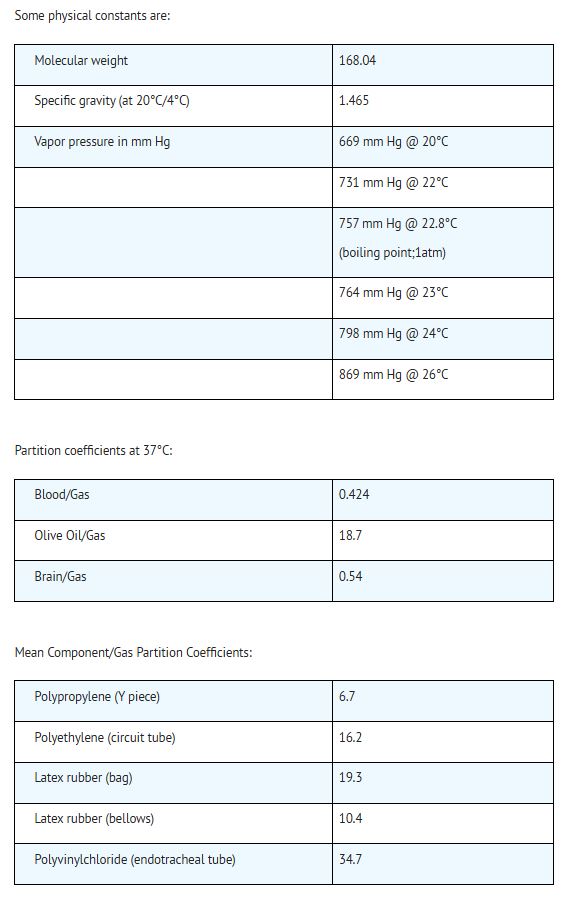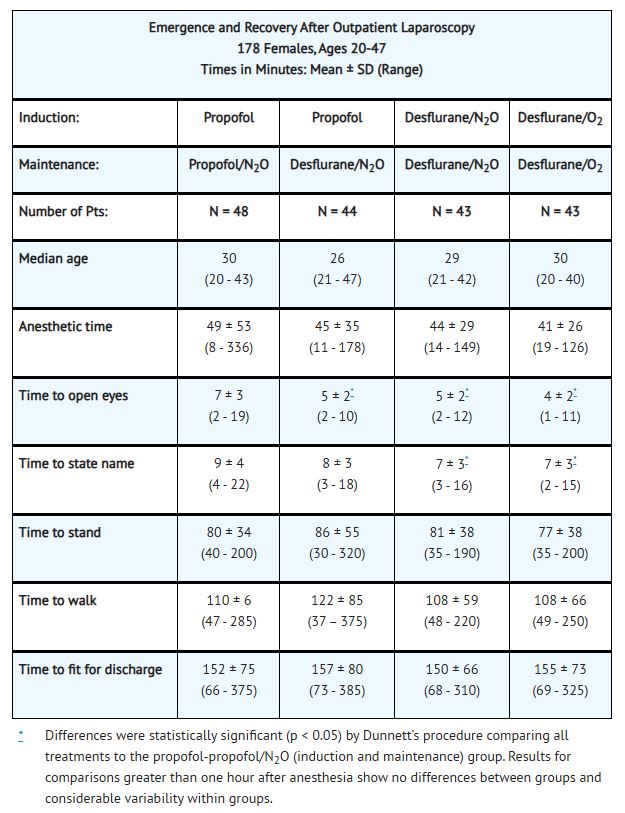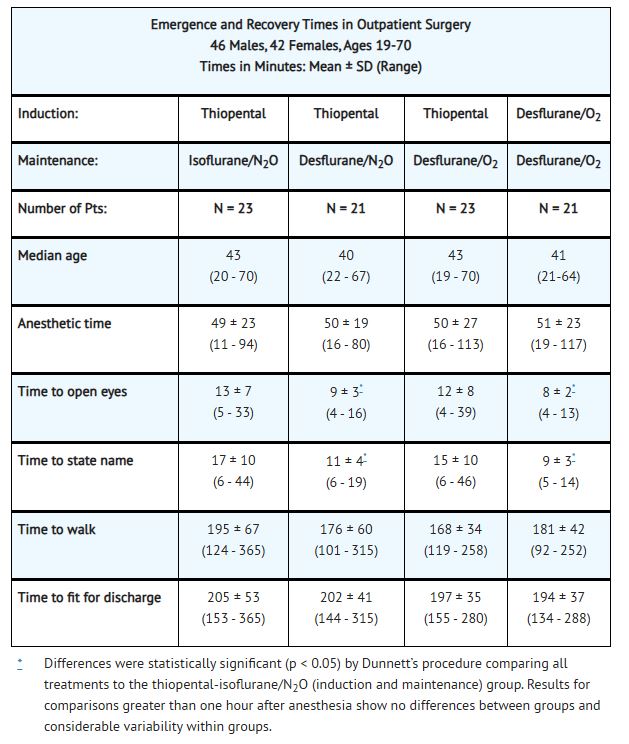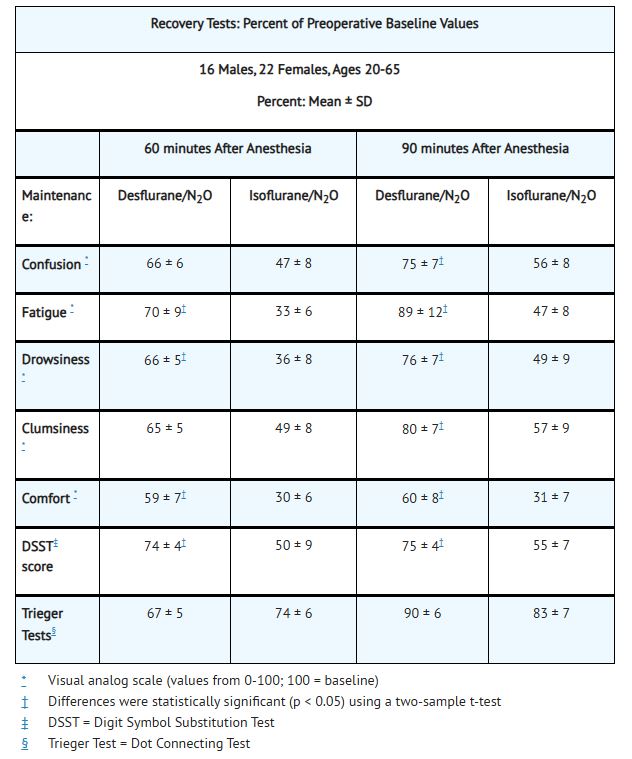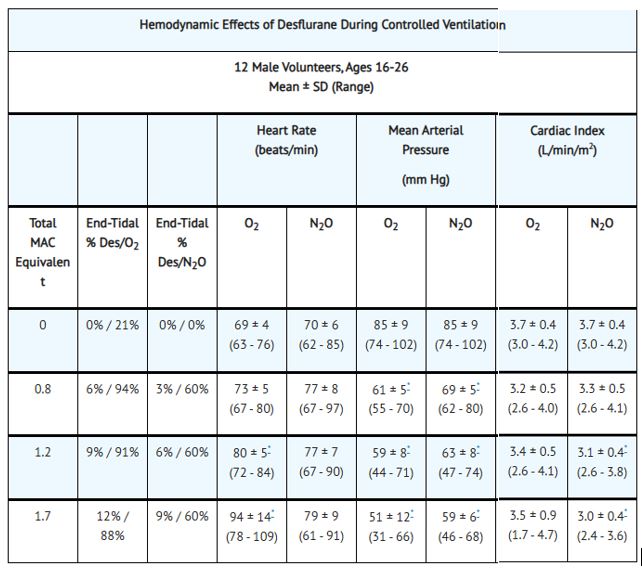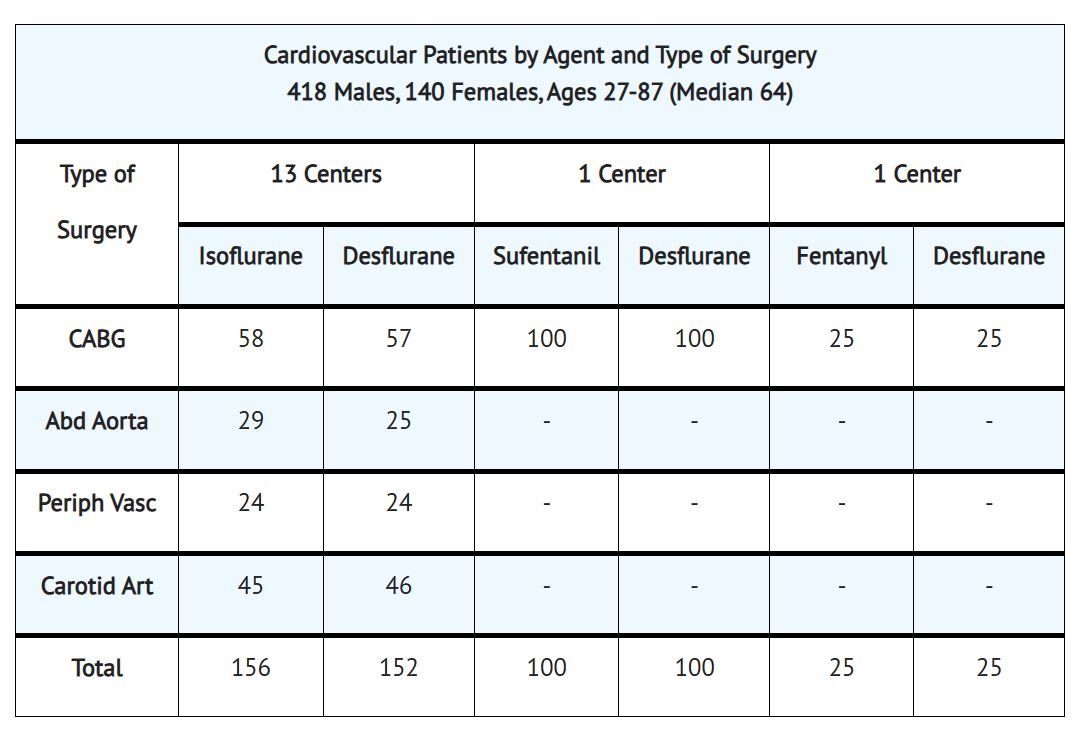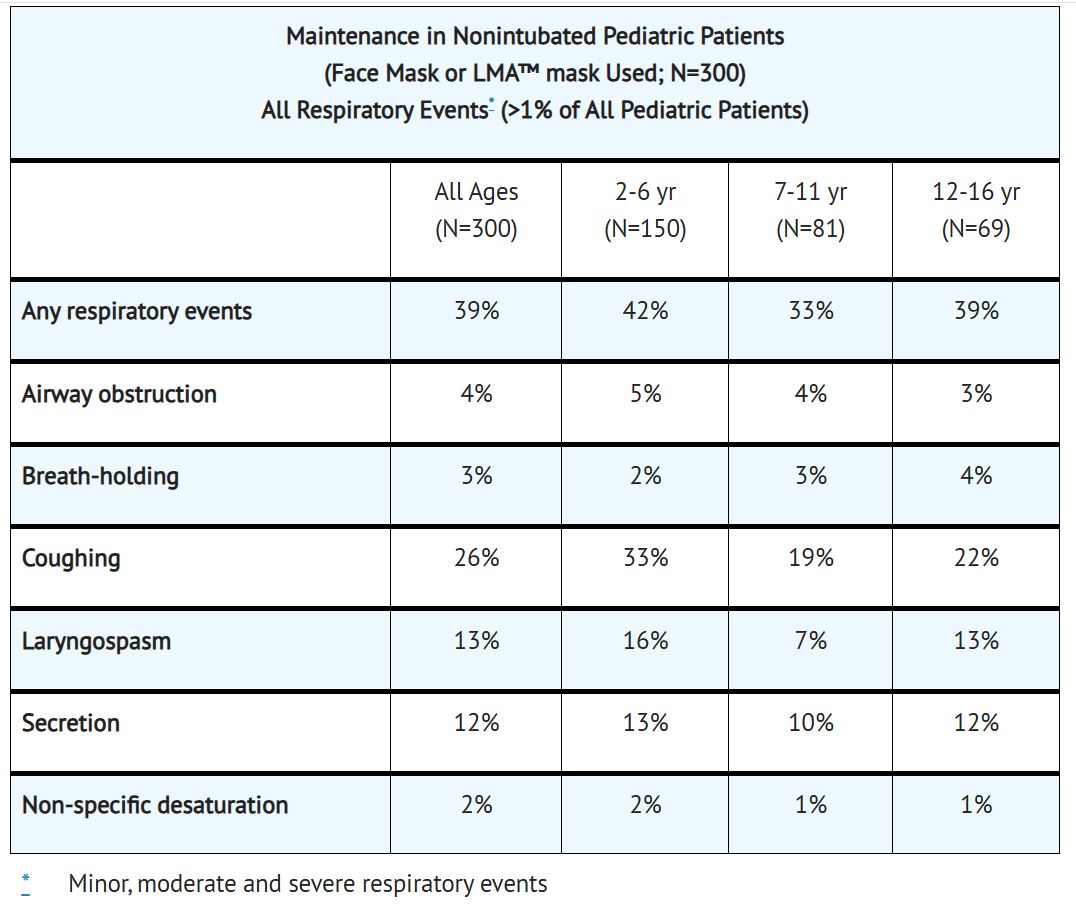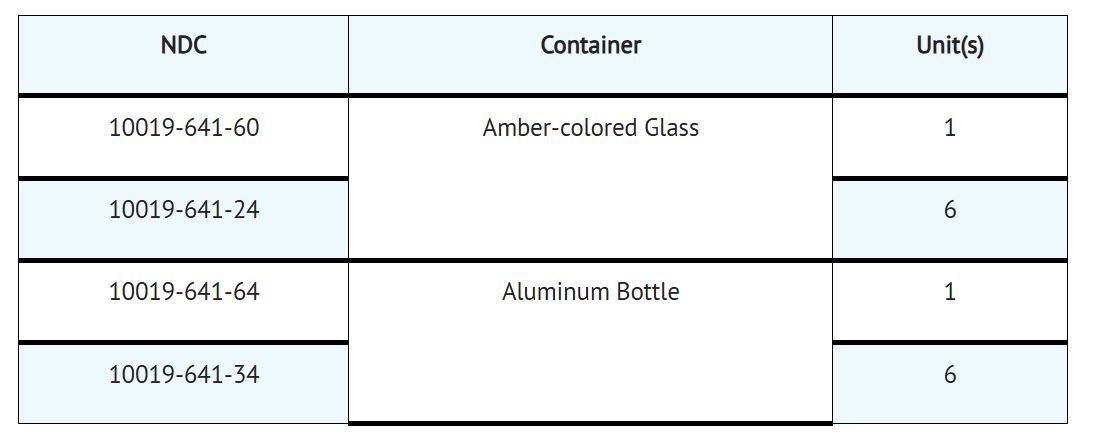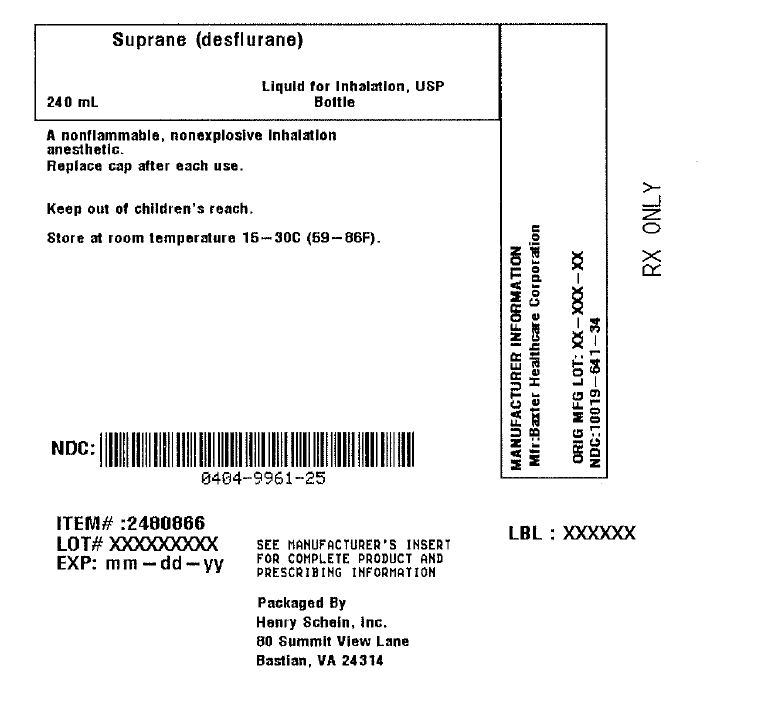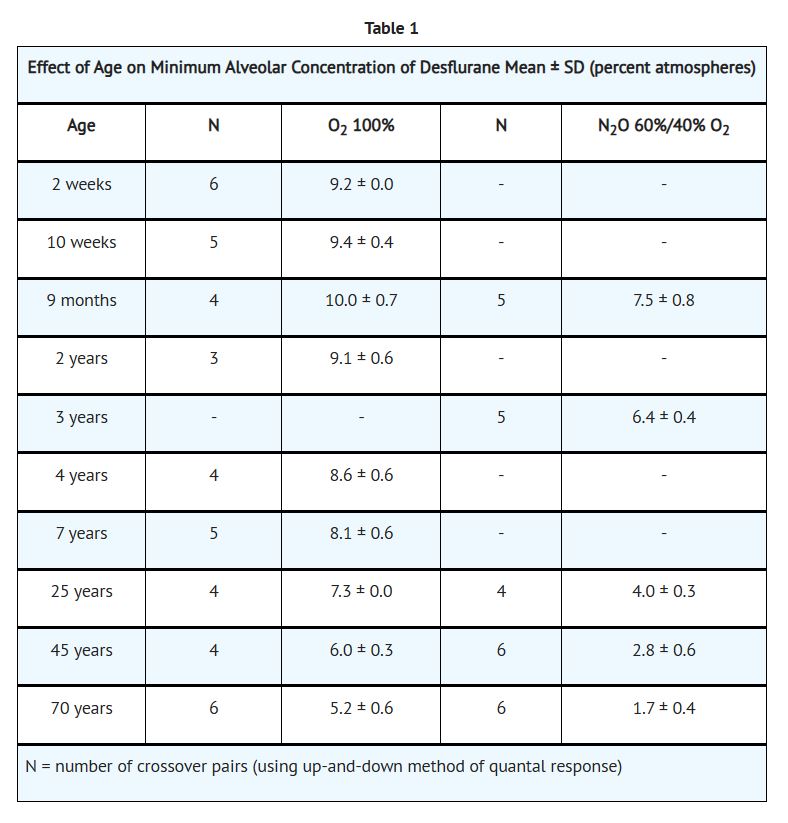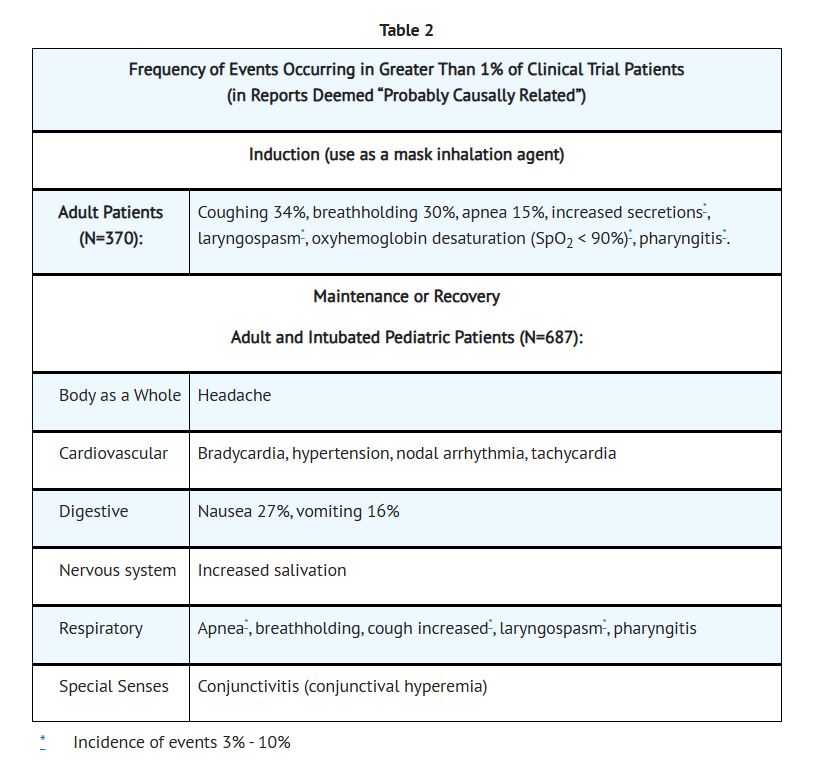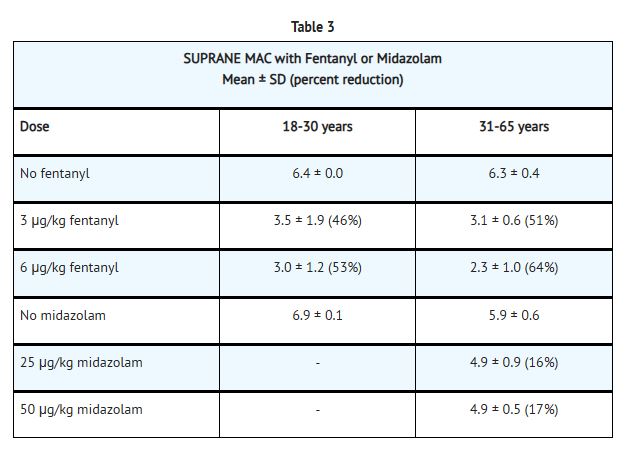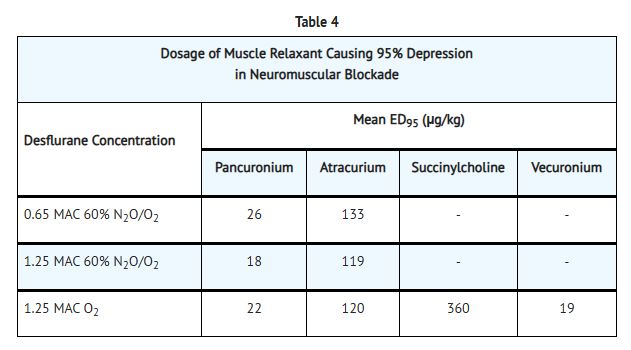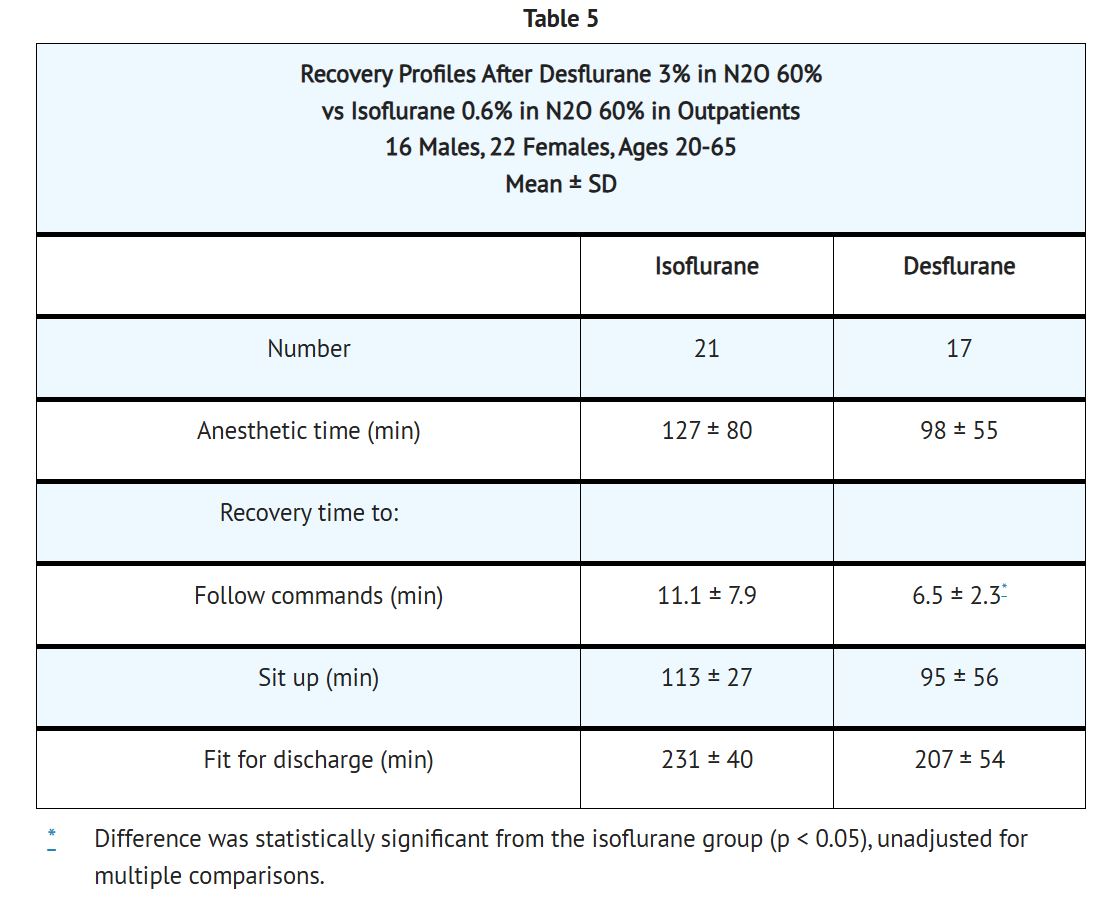 DRUG LABEL: Suprane
NDC: 0404-9961 | Form: LIQUID
Manufacturer: Henry Schein, Inc.
Category: prescription | Type: HUMAN PRESCRIPTION DRUG LABEL
Date: 20251107

ACTIVE INGREDIENTS: Desflurane 240 mL/240 mL

HIGHLIGHTS OF PRESCRIBING INFORMATION

Suprane
(desflurane, USP)
Volatile Liquid for Inhalation
These highlights do not include all the information needed to use SUPRANE safely and effectively. See full prescribing information for SUPRANE.SUPRANE (desflurane) liquid, for inhalation use
Initial U.S. Approval: 1992

RECENT MAJOR CHANGES

Contraindications (4) 11/2022

Warnings and Precautions; Malignant Hyperthermia (5.1) 11/2022

1. INDICATIONS AND USAGE

Suprane is an inhalation agent indicated:

- for induction and/or maintenance of anesthesia in adults (1.1)
- for maintenance of anesthesia in pediatric patients following induction with agents other than Suprane and intubation.

2. DOSAGE AND ADMINISTRATION

• SUPRANE should be administered only by persons trained in the administration of general anesthesia. It should only be administered using a vaporizer specifically designed and designated for use with SUPRANE. (2)
• The administration of general anesthesia must be individualized based on the patient’s response, including cardiovascular and pulmonary changes. (2)
• SUPRANE should not be used as the sole agent for anesthetic induction in patients with coronary artery disease or where increases in heart rate or blood pressure are undesirable. (2.6)
• For dosing considerations in patients with intracranial space occupying lesions, see Full Prescribing Information. (2.7)

3. DOSAGE FORMS AND STRENGTHS

• Liquid (volatile): 100% (3)

4. CONTRAINDICATIONS

• Patients with known or suspected genetic susceptibility to malignant hyperthermia (4)
• Patients in whom general anesthesia is contraindicated (4)
• Induction of anesthesia in pediatric patients (4)
• Patients with known sensitivity to halogenated agents (4)
• Patients with a history of moderate to severe hepatic dysfunction following anesthesia with halogenated agents and not otherwise explained. (4)

5. WARNINGS AND PRECAUTIONS

• Malignant Hyperthermia: Malignant hyperthermia may occur, especially in individuals with known or suspected susceptibility based on genetic factors or family history. Discontinue triggering agents, administer intravenous dantrolene sodium, and apply supportive therapies. (5.1)
• Perioperative Hyperkalemia: Perioperative hyperkalemia may occur. Patients with latent or overt neuromuscular disease, particularly with Duchenne muscular dystrophy, appear to be most vulnerable. Early, aggressive intervention is recommended. (5.2)
• Respiratory Adverse Reactions in Pediatric Patients:
- Not approved for maintenance of anesthesia in non-intubated children due to an increased incidence of respiratory adverse reactions. Monitor and treat accordingly.(5.3)
- May cause airway narrowing and increased airway resistance in children with asthma or a history of recent upper airway infection. Monitor and treat accordingly.(5.3)
• QT Prolongation: Carefully monitor cardiac rhythm when administering SUPRANE to susceptible patients. (5.4)
• Interactions with Desiccated Carbon Dioxide (CO2) Absorbents: May react with desiccated CO2 absorbents to produce carbon monoxide. Replace desiccated CO2 absorbent before administration of SUPRANE. (5.5)
• Hepatobiliary Disorders: May cause sensitivity hepatitis in patients sensitized by previous exposure to halogenated anesthetics. Approach repeated anesthesia with caution. (5.6)
• Pediatric Neurotoxicity: In developing animals, exposures greater than 3 hours cause neurotoxicity. Weigh benefits against potential risks when considering elective procedures in children under 3 years old. (5.7)
• Postoperative Agitation in Children: May cause postoperative agitation during emergence from anesthesia in children. (5.9)

6. ADVERSE REACTIONS

Most common adverse reactions (incidence> 10%) are coughing, breath holding, apnea, nausea, vomiting. (6)

To report SUSPECTED ADVERSE REACTIONS, contact Baxter Healthcare Corporation at 1-800-262-3784 or FDA at 1-800-FDA-1088 or www.fda.gov/medwatch.

7. DRUG INTERACTIONS

• Concomitant use of N2O, benzodiazepines and/or opioids reduces the MAC of SUPRANE. Adjust dose accordingly. (7.1, 7.3)
• SUPRANE decreases the doses of neuromuscular blocking agents required. Adjust dose accordingly. (7.2)

8. USE IN SPECIFIC POPULATIONS

- Geriatric Use: The minimum alveolar concentration (MAC) of SUPRANE decreases with increasing patient age. (8.5)

See 17 for PATIENT COUNSELING INFORMATION.

Revised: 02/2023

FULL PRESCRIBING INFORMATION

1. INDICATIONS AND USAGE

1.1 Induction of Anesthesia
SUPRANE is indicated as an inhalation agent for induction of anesthesia for inpatient and outpatient surgery in adults.

SUPRANE is contraindicated as an inhalation agent for the induction of anesthesia in pediatric patients because of a high incidence of moderate to severe upper airway adverse events.

1.2 Maintenance of Anesthesia
SUPRANE is indicated as an inhalation agent for maintenance of anesthesia for inpatient and outpatient surgery in adults and in pediatric patients.

After induction of anesthesia with agents other than SUPRANE, and tracheal intubation, SUPRANE is indicated for maintenance of anesthesia in infants and children. SUPRANE is not approved for maintenance of anesthesia in non-intubated children due to an increased incidence of respiratory adverse reactions, including coughing, laryngospasm, and secretions [See WARNINGS AND PRECAUTIONS (5.3) and CLINICAL STUDIES (14.5)].

2. DOSAGE AND ADMINISTRATION

Only persons trained in the administration of general anesthesia should administer SUPRANE. Only a vaporizer specifically designed and designated for use with desflurane should be utilized for its administration. Facilities for maintenance of a patent airway, artificial ventilation, oxygen enrichment, and circulatory resuscitation must be immediately available.

SUPRANE is administered by inhalation. The administration of general anesthesia must be individualized based on the patient’s response. Hypotension and respiratory depression increase as anesthesia with SUPRANE is deepened. The minimum alveolar concentration (MAC) of SUPRANE decreases with increasing patient age. The MAC for SUPRANE is also reduced by concomitant N2O administration (see Table 1). The dose should be adjusted accordingly. The following table provides mean relative potency based upon age and effect of N2O in predominately ASA physical status I or II patients.

Benzodiazepines and opioids decrease the MAC of SUPRANE [See Drug Interactions (7.1, Table 3)]. SUPRANE also decreases the doses of neuromuscular blocking agents required [See Drug Interactions (7.2, Table 4)]. The dose should be adjusted accordingly.

2.1 Preanesthetic Medication
Issues such as whether or not to premedicate and the choice of premedication(s) must be individualized. In clinical studies, patients scheduled to be anesthetized with SUPRANE frequently received IV preanesthetic medication, such as opioid and/or benzodiazepine.

2.2 Induction
In adults, some premedicated with opioid, a frequent starting concentration was 3% SUPRANE, increased in 0.5-1.0% increments every 2 to 3 breaths. End-tidal concentrations of 4-11%, SUPRANE with and without N2O, produced anesthesia within 2 to 4 minutes. When SUPRANE was tested as the primary anesthetic induction agent, the incidence of upper airway irritation (apnea, breathholding, laryngospasm, coughing and secretions) was high. During induction in adults, the overall incidence of oxyhemoglobin desaturation (SpO2 < 90%) was 6% [See Adverse Reactions (6.1)].

After induction in adults with an intravenous drug such as thiopental or propofol, SUPRANE can be started at approximately 0.5-1 MAC, whether the carrier gas is O2 or N2O/O2.

Inspired concentrations of SUPRANE greater than 12% have been safely administered to patients, particularly during induction of anesthesia. Such concentrations will proportionately dilute the concentration of oxygen; therefore, maintenance of an adequate concentration of oxygen may require a reduction of nitrous oxide or air if these gases are used concurrently.

2.3 Maintenance
Surgical levels of anesthesia in adults may be maintained with concentrations of 2.5-8.5% SUPRANE with or without the concomitant use of nitrous oxide. In children, surgical levels of anesthesia may be maintained with concentrations of 5.2-10% SUPRANE with or without the concomitant use of nitrous oxide.

During the maintenance of anesthesia with inflow rates of 2 L/min or more, the alveolar concentration of SUPRANE will usually be within 10% of the inspired concentration [FA/F1, See Figure 2 in Clinical Pharmacology (12.3)].

During the maintenance of anesthesia, increasing concentrations of SUPRANE produce dose-dependent decreases in blood pressure. Excessive decreases in blood pressure may be due to depth of anesthesia and in such instances may be corrected by decreasing the inspired concentration of SUPRANE.

Concentrations of SUPRANE exceeding 1 MAC may increase heart rate. Thus with this drug, an increased heart rate may not serve reliably as a sign of inadequate anesthesia.

2.4 Maintenance of Anesthesia in Intubated Pediatric Patients
SUPRANE is indicated for maintenance of anesthesia in infants and children after induction of anesthesia with agents other than SUPRANE, and tracheal intubation.

SUPRANE, with or without N2O, and halothane, with or without N2O were studied in three clinical trials of pediatric patients aged 2 weeks to 12 years (median 2 years) and ASA physical status I or II. The concentration of SUPRANE required for maintenance of general anesthesia is age-dependent [See Clinical Studies (14.5)].

Changes in blood pressure during maintenance of and recovery from anesthesia with SUPRANE /N2O/O2 are similar to those observed with halothane/N2O/O2. Heart rate during maintenance of anesthesia is approximately 10 beats per minute faster with SUPRANE than with halothane. Patients were judged fit for discharge from post-anesthesia care units within one hour with both SUPRANE and halothane. There were no differences in the incidence of nausea and vomiting between patients receiving SUPRANE or halothane.

2.5 Recovery
The recovery from general anesthesia should be assessed carefully before patients are discharged from the post anesthesia care unit (PACU).

2.6 Use in Patients with Coronary Artery Disease
In patients with coronary artery disease, maintenance of normal hemodynamics is important to prevent myocardial ischemia. A rapid increase in desflurane concentration is associated with marked increase in pulse rate, mean arterial pressure and levels of epinephrine and norepinephrine. SUPRANE should not be used as the sole agent for anesthetic induction in patients with coronary artery disease or patients where increases in heart rate or blood pressure are undesirable. It should be used with other medications, preferably intravenous opioids and hypnotics [See Clinical Studies (14.2)].

2.7 Neurosurgical Use
SUPRANE may produce a dose-dependent increase in cerebrospinal fluid pressure (CSFP) when administered to patients with intracranial space occupying lesions. SUPRANE should be administered at 0.8 MAC or less, and in conjunction with a barbiturate induction and hyperventilation (hypocapnia) until cerebral decompression in patients with known or suspected increases in CSFP. Appropriate attention must be paid to maintain cerebral perfusion pressure [See Clinical Studies (14.4)].

2.8 Observations Related to Vaporizer Use
Yellow discoloration of SUPRANE sometimes accompanied by particulates, has been observed through the vaporizer sight glass or after draining the vaporizer. The presence of discoloration or particulates in these situations does not alter the quality or efficacy of SUPRANE. If observed, refer to the respective vaporizer Instructions For Use (IFU) for recommended actions or contact Baxter Product Surveillance.

3. DOSAGE FORMS AND STRENGTHS

SUPRANE (desflurane, USP) is a colorless, non-flammable, volatile liquid (below 22.8°C) for inhalation, 100% desflurane.

4. CONTRAINDICATIONS

The use of SUPRANE is contraindicated in the following conditions:

• Known or suspected genetic susceptibility to malignant hyperthermia [see Warnings and Precautions (5.1), Clinical Pharmacology (12.5)].
• Patients in whom general anesthesia is contraindicated.
• Induction of anesthesia in pediatric patients.
• Patients with known sensitivity to SUPRANE or to other halogenated agents [See Warnings and Precautions (5.5)].
• Patients with a history of moderate to severe hepatic dysfunction following anesthesia with SUPRANE or other halogenated agents and not otherwise explained [See Warnings and Precautions (5.5)].

5. WARNINGS AND PRECAUTIONS

5.1 Malignant Hyperthermia
In susceptible individuals, volatile anesthetic agents, including desflurane, may trigger malignant hyperthermia, a skeletal muscle hypermetabolic state leading to high oxygen demand. Fatal outcomes of malignant hyperthermia have been reported.

The risk of developing malignant hyperthermia increases with the concomitant administration of succinylcholine and volatile anesthetic agents. SUPRANE can induce malignant hyperthermia in patients with known or suspected susceptibility based on genetic factors or family history, including those with certain inherited ryanodine receptor (RYR1) or dihydropyridine receptor (CACNA1S) variants. [see Contraindications (4), Clinical Pharmacology (12.5)]

Signs consistent with malignant hyperthermia may include hyperthermia, hypoxia, hypercapnia, muscle rigidity (e.g., jaw muscle spasm), tachycardia (e.g., particularly that unresponsive to deepening anesthesia or analgesic medication administration), tachypnea, cyanosis, arrhythmias, hypovolemia, and hemodynamic instability. Skin mottling, coagulopathies, and renal failure may occur later in the course of the hypermetabolic process.

Successful treatment of malignant hyperthermia depends on early recognition of the clinical signs. If malignant hyperthermia is suspected, discontinue all triggering agents (i.e., volatile anesthetic agents and succinylcholine), administer intravenous dantrolene sodium, and initiate supportive therapies. Consult prescribing information for intravenous dantrolene sodium for additional information on patient management. Supportive therapies include administration of supplemental oxygen and respiratory support based on clinical need, maintenance of hemodynamic stability and adequate urinary output, management of fluid and electrolyte balance, correction of acid basederangements, and institution of measures to control rising temperature.

5.2 Perioperative Hyperkalemia
Use of inhaled anesthetic agents has been associated with rare increases in serum potassium levels that have resulted in cardiac arrhythmias and death in pediatric patients during the postoperative period. Patients with latent as well as overt neuromuscular disease, particularly Duchenne muscular dystrophy, appear to be most vulnerable. Concomitant use of succinylcholine has been associated with most, but not all, of these cases. These patients also experienced significant elevations in serum creatinine kinase levels and, in some cases, changes in urine consistent with myoglobinuria. Despite the similarity in presentation to malignant hyperthermia, none of these patients exhibited signs or symptoms of muscle rigidity or hypermetabolic state. Early and aggressive intervention to treat the hyperkalemia and resistant arrhythmias is recommended, as is subsequent evaluation for latent neuromuscular disease.

5.3 Respiratory Adverse Reactions in Pediatric Patients
SUPRANE is not approved for maintenance of anesthesia in non-intubated children due to an increased incidence of respiratory adverse reactions, including coughing, laryngospasm and secretions [See Clinical Studies (14.5)].

Children, particularly if 6 years old or younger, who are under an anesthetic maintenance of SUPRANE delivered via laryngeal mask airway (LMA™ mask) are at increased risk for adverse respiratory reactions, e.g., coughing and laryngospasm, especially with removal of the laryngeal mask airway under deep anesthesia [See Clinical Studies (14.5)]. Therefore, closely monitor these patients for signs and symptoms associated with laryngospasm and treat accordingly.

When SUPRANE is used for maintenance of anesthesia in children with asthma or a history of recent upper airway infection, there is an increased risk for airway narrowing and increases in airway resistance. Therefore, closely monitor these patients for signs and symptoms associated with airway narrowing and treat accordingly.

5.4 QT Prolongation
QT prolongation, associated with torsade de pointes, has been reported [see Adverse Reactions (6.2)]. Carefully monitor cardiac rhythm when administering SUPRANE to susceptible patients (e.g., patients with congenital Long QT Syndrome or patients taking drugs that can prolong the QT interval).

5.5 Interactions with Desiccated Carbon Dioxide Absorbents
Desflurane like some other inhalation anesthetics, can react with desiccated carbon dioxide (CO2) absorbents to produce carbon monoxide that may result in elevated levels of carboxyhemoglobin in some patients. Case reports suggest that barium hydroxide lime and soda lime become desiccated when fresh gases are passed through the CO2 canister at high flow rates over many hours or days. When a clinician suspects that CO2 absorbent may be desiccated, it should be replaced before the administration of SUPRANE.

5.6 Hepatobiliary Disorders
With the use of halogenated anesthetics, disruption of hepatic function, icterus and fatal liver necrosis have been reported; such reactions appear to indicate hypersensitivity. As with other halogenated anesthetic agents, SUPRANE may cause sensitivity hepatitis in patients who have been sensitized by previous exposure to halogenated anesthetics [See Contraindications (4)]. Cirrhosis, viral hepatitis or other pre-existing hepatic disease may be a reason to select an anesthetic other than a halogenated anesthetic. As with all halogenated anesthetics, repeated anesthesia within a short period of time should be approached with caution.

5.7 Pediatric Neurotoxicity
Published animal studies demonstrate that the administration of anesthetic and sedation drugs that block NMDA receptors and/or potentiate GABA activity increase neuronal apoptosis in the developing brain and result in long-term cognitive deficits when used for longer than 3 hours. The clinical significance of these findings is not clear. However, based on the available data, the window of vulnerability to these changes is believed to correlate with exposures in the third trimester of gestation through the first several months of life, but may extend out to approximately three years of age in humans. [See Use in Specific Populations (8.1, 8.4), Nonclinical Toxicology (13.2)].

Some published studies in children suggest that similar deficits may occur after repeated or prolonged exposures to anesthetic agents early in life and may result in adverse cognitive or behavioral effects. These studies have substantial limitations, and it is not clear if the observed effects are due to the anesthetic/sedation drug administration or other factors such as the surgery or underlying illness.

Anesthetic and sedation drugs are a necessary part of the care of children needing surgery, other procedures, or tests that cannot be delayed, and no specific medications have been shown to be safer than any other. Decisions regarding the timing of any elective procedures requiring anesthesia should take into consideration the benefits of the procedure weighed against the potential risks.

5.8 Laboratory Findings
Transient elevations in glucose and white blood cell count may occur as with use of other anesthetic agents.

5.9 Postoperative Agitation in Children
Emergence from anesthesia in children may evoke a brief state of agitation that may hinder cooperation.

6. ADVERSE REACTIONS

6.1 Clinical Trials Experience
Because clinical trials are conducted under widely varying conditions, adverse reaction rates observed in the clinical trials of a drug cannot be directly compared to rates in the clinical trials of another drug and may not reflect the rates observed in practice.

Adverse event information is derived from controlled clinical trials, the majority of which were conducted in the United States. The studies were conducted using a variety of premedications, other anesthetics, and surgical procedures of varying length. Most adverse events reported were mild and transient, and may reflect the surgical procedures, patient characteristics (including disease) and/or medications administered.

Of the 2,143 patients exposed to SUPRANE in clinical trials, 370 adults and 152 children were induced with desflurane alone and 987 patients were maintained principally with desflurane. The frequencies given reflect the percent of patients with the event. Each patient was counted once for each type of adverse event. They are presented in alphabetical order according to body system.

6.2 Post-Marketing Experience
The following adverse reactions have been identified during post-approval use of SUPRANE. Because these reactions are reported voluntarily from a population of uncertain size, it is not possible to reliably estimate their frequency or establish a causal relationship to drug exposure.

Blood and Lymphatic System Disorders: Coagulopathy

Metabolism and Nutrition Disorders: Hyperkalemia, Hypokalemia, metabolic acidosis

Psychiatric Disorders: Delirium

Nervous System Disorders: Convulsion, Post-operative agitation in children

Eye Disorders: Ocular icterus

Cardiac Disorders: Cardiac arrest, electrocardiogram QT prolonged, torsade de pointes, ventricular failure, ventricular hypokinesia, atrial fibrillation

Vascular Disorders: Malignant hypertension, hemorrhage, hypotension, shock

Respiratory, Thoracic and Mediastinal Disorders: Respiratory arrest, respiratory failure, respiratory distress, bronchospasm, hemoptysis

Gastrointestinal Disorders: Pancreatitis acute, abdominal pain

Hepatobiliary Disorders: Hepatic failure, hepatic necrosis, hepatitis, cytolytic hepatitis, cholestasis, jaundice, hepatic function abnormal, liver disorder

Skin and Subcutaneous Tissue Disorder: Urticaria, erythema

Musculoskeletal, Connective Tissue and Bone Disorders: Rhabdomyolysis

General Disorders and Administration Site Conditions: Hyperthermia malignant, asthenia, malaise

Investigations: Electrocardiogram ST-T change, electrocardiogram T-wave inversion, tranaminases increased, alanine aminotransferase increased, aspartate aminotransferase increased, blood bilirubin increased, coagulation test abnormal, ammonia increased

Injury, Poisoning, and Procedural Complications*: Tachyarrhythmia, palpitations, eye burns, blindness transient, encephalopathy, ulcerative keratitis, ocular hyperemia, visual acuity reduced, eye irritation, eye pain, dizziness, migraine, fatigue, accidental exposure, skin burning sensation, drug administration error

*Reactions categorized within this System Organ Class (SOC) were accidental exposures to non-patients.

7. DRUG INTERACTIONS

No clinically significant adverse interactions with commonly used preanesthetic drugs, or drugs used during anesthesia (muscle relaxants, intravenous agents, and local anesthetic agents) were reported in clinical trials. The effect of SUPRANE on the disposition of other drugs has not been determined. Similar to isoflurane, SUPRANE does not predispose to premature ventricular arrhythmias in the presence of exogenously infused epinephrine in swine.

7.1 Benzodiazepines and Opioids (MAC Reduction)
Benzodiazepines and opioids decrease the amount of desflurane (MAC) needed to produce anesthesia. This effect is shown in Table 3 for intravenous midazolam (25-50 µg/kg) and intravenous fentanyl (3-6 µg/kg) in patients of two different age groups.

7.2 Neuromuscular Blocking Agents

Anesthetic concentrations of desflurane at equilibrium (administered for 15 or more minutes before testing) reduced the ED95 of succinylcholine by approximately 30% and that of atracurium and pancuronium by approximately 50% compared to N2O/opioid anesthesia (see Table 4). The effect of desflurane on duration of nondepolarizing neuromuscular blockade has not been studied.

Dosage reduction of neuromuscular blocking agents during induction of anesthesia may result in delayed onset of conditions suitable for endotracheal intubation or inadequate muscle relaxation, because potentiation of neuromuscular blocking agents requires equilibration of muscle with the delivered partial pressure of SUPRANE.

Among nondepolarizing drugs, pancuronium, atracurium, and vecuronium interactions have been studied. In the absence of specific guidelines:

1. For endotracheal intubation, do not reduce the dose of nondepolarizing muscle relaxants or succinylcholine.
2. During maintenance of anesthesia, the dose of nondepolarizing muscle relaxants is likely to be reduced compared to that during N2O/opioid anesthesia. Administration of supplemental doses of muscle relaxants should be guided by the response to nerve stimulation.

7.3 Concomitant use with N2O
Concomitant administration of N2O reduces the MAC of SUPRANE [See Dosage and Administration (2), Table 1].

8. USE IN SPECIFIC POPULATIONS

8.1 Pregnancy
Risk Summary

There are no adequate and well-controlled studies in pregnant women. In animal reproduction studies, embryo-fetal toxicity (reduced viable fetuses and/or increased post-implantation loss) was noted in pregnant rats and rabbits administered 1 MAC desflurane for 4 hours a day (4 MAC-hours/day) during organogenesis.

Published studies in pregnant primates demonstrate that the administration of anesthetic and sedation drugs that block NMDA receptors and/or potentiate GABA activity during the period of peak brain development increases neuronal apoptosis in the developing brain of the offspring when used for longer than 3 hours. There are no data on pregnancy exposures in primates corresponding to periods prior to the third trimester in humans [See Data].

The estimated background risk of major birth defects and miscarriage for the indicated population is unknown. All pregnancies have a background risk of birth defect, loss, or other adverse outcomes. In the U.S. general population, the estimated background risk of major birth defects and miscarriage in clinically recognized pregnancies is 2-4% and 15- 20%, respectively.

Clinical Considerations

Labor or Delivery

The safety of SUPRANE during labor or delivery has not been demonstrated. SUPRANE is a uterine-relaxant.

Data

Animal Data

Pregnant rats were exposed to 8.2% desflurane (1 MAC; 60% oxygen) for 0.5, 1.0, or 4.0 hours (0.5, 1.0, or 4.0 MAC-hours) per day during organogenesis (Gestation Day 6-15).

Embryo-fetal toxicity (increased post-implantation loss and reduced viable fetuses) was noted in the 4 hour treatment group in the presence of maternal toxicity (reduced body weight gain). There was no evidence of malformations in any group.

Pregnant rabbits were exposed to 8.9% desflurane (1 MAC; 60% oxygen) for 0.5, 1.0, or 3.0 hours per day during organogenesis (Gestation Days 6-18). Fetal toxicity (reduced viable fetuses) was noted in the 3 hour treatment group in the presence of maternal toxicity (reduced body weight). There was no evidence of malformations in any group.

Pregnant rats were exposed to 8.2% desflurane (1 MAC; 60% oxygen) for 0.5, 1.0, or 4.0 hours per day from late gestation and through lactation (Gestation Day 15 to Lactation Day 21). Pup body weights were reduced in the 4 hours per day group in the presence of maternal toxicity (increased mortality and reduced body weight gain). This study did not evaluate neurobehavioral function including learning and memory or reproductive behavior in the first generation (F1) pups.

In a published study in primates, administration of an anesthetic dose of ketamine for 24 hours on Gestation Day 122 increased neuronal apoptosis in the developing brain of the fetus. In other published studies, administration of either isoflurane or propofol for 5 hours on Gestation Day 120 resulted in increased neuronal and oligodendrocyte apoptosis in the developing brain of the offspring. With respect to brain development, this time period corresponds to the third trimester of gestation in the human. The clinical significance of these findings is not clear; however, studies in juvenile animals suggest neuroapoptosis correlates with long-term cognitive deficits [See Warnings and Precautions (5.6), Use in Specific Populations (8.4), and Nonclinical Toxicology (13.2)].

8.2 Lactation
It is not known whether this drug is excreted in human milk. Because many drugs are excreted in human milk, caution should be exercised when SUPRANE is administered to a nursing woman.

8.4 Pediatric Use
Respiratory Adverse Reactions in Pediatric Patients

SUPRANE is indicated for maintenance of anesthesia in infants and children after induction of anesthesia with agents other than SUPRANE, and tracheal intubation.

Is not approved for maintenance of anesthesia in non-intubated children due to an increased incidence of respiratory adverse reactions, including coughing (26%), laryngospasm (13%) and secretions (12%) [See Clinical Studies (14.5)].

Children, particularly if 6 years old or younger, who are under an anesthetic maintenance of SUPRANE delivered via laryngeal mask airway (LMA™ mask) are at increased risk for adverse respiratory reactions, e.g., coughing and laryngospasm, especially with removal of the laryngeal mask airway under deep anesthesia [See Clinical Studies (14.5)]. Therefore, closely monitor these patients for signs and symptoms associated with laryngospasm and treat accordingly.

When SUPRANE is used for maintenance of anesthesia in children with asthma or a history of recent upper airway infection, there is an increased risk for airway narrowing and increases in airway resistance. Therefore, closely monitor these patients for signs and symptoms associated with airway narrowing and treat accordingly.

Published juvenile animal studies demonstrate that the administration of anesthetic and sedation drugs, such as SUPRANE, that either block NMDA receptors or potentiate the activity of GABA during the period of rapid brain growth or synaptogenesis, results in widespread neuronal and oligodendrocyte cell loss in the developing brain and alterations in synaptic morphology and neurogenesis. Based on comparisons across species, the window of vulnerability to these changes is believed to correlate with exposures in the third trimester of gestation through the first several months of life, but may extend out to approximately 3 years of age in humans.

In primates, exposure to 3 hours of ketamine that produced a light surgical plane of anesthesia did not increase neuronal cell loss, however, treatment regimens of 5 hours or longer of isoflurane increased neuronal cell loss. Data from isoflurane-treated rodents and ketamine-treated primates suggest that the neuronal and oligodendrocyte cell losses are associated with prolonged cognitive deficits in learning and memory. The clinical significance of these nonclinical findings is not known, and healthcare providers should balance the benefits of appropriate anesthesia in pregnant women, neonates, and young children who require procedures with the potential risks suggested by the nonclinical data [See Warnings and Precautions (5.6), Use in Specific Populations (8.1), and Nonclinical Toxicology (13.2)].

8.5 Geriatric Use
The minimum alveolar concentration (MAC) of SUPRANE decreases with increasing patient age. The dose should be adjusted accordingly. The average MAC for SUPRANE in a 70 year old patient is two-thirds the MAC for a 20 year old patient [See Dosage and Administration (2) Table 1 and Clinical Studies (14.3)].

8.6 Renal Impairment
Concentrations of 1-4% SUPRANE in nitrous oxide/oxygen have been used in patients with chronic renal or hepatic impairment and during renal transplantation surgery.

Because of minimal metabolism, a need for dose adjustment in patients with renal and hepatic impairment is not to be expected.

Nine patients receiving desflurane (N=9) were compared to 9 patients receiving isoflurane, all with chronic renal insufficiency (serum creatinine 1.5-6.9 mg/dL). No differences in hematological or biochemical tests, including renal function evaluation, were seen between the two groups. Similarly, no differences were found in a comparison of patients receiving either desflurane (N=28) or isoflurane (N=30) undergoing renal transplant.

8.7 Hepatic Impairment
Eight patients receiving SUPRANE were compared to six patients receiving isoflurane, all with chronic hepatic disease (viral hepatitis, alcoholic hepatitis, or cirrhosis). No differences in hematological or biochemical tests, including hepatic enzymes and hepatic function evaluation, were seen.

10. OVERDOSAGE

The symptoms of overdosage of SUPRANE can present as a deepening of anesthesia, cardiac and/or respiratory depression in spontaneously breathing patients, and cardiac depression in ventilated patients in whom hypercapnia and hypoxia may occur only at a late stage. In the event of overdosage, or suspected overdosage, take the following actions: discontinue administration of SUPRANE, maintain a patent airway, initiate assisted or controlled ventilation with oxygen, and maintain adequate cardiovascular function.

11. DESCRIPTION

SUPRANE (desflurane, USP), a nonflammable liquid administered via vaporizer, is a general inhalation anesthetic. It is (±)1,2,2,2-tetrafluoroethyl difluoromethyl ether:

SUPRANE is nonflammable as defined by the requirements of International Electrotechnical Commission 601-2-13.

SUPRANE is a colorless, volatile liquid below 22.8°C. Data indicate that SUPRANE is stable when stored under normal room lighting conditions according to instructions.

SUPRANE is chemically stable. The only known degradation reaction is through prolonged direct contact with soda lime producing low levels of fluoroform (CHF3). The amount of CHF3 obtained is similar to that produced with MAC-equivalent doses of isoflurane. No discernible degradation occurs in the presence of strong acids.

SUPRANE does not corrode stainless steel, brass, aluminum, anodized aluminum, nickel plated brass, copper, or beryllium.

12. CLINICAL PHARMACOLOGY

12.2 Pharmacodynamics
Changes in the clinical effects of SUPRANE rapidly follow changes in the inspired concentration. The duration of anesthesia and selected recovery measures for SUPRANE are given in the following tables:

In 178 female outpatients undergoing laparoscopy, premedicated with fentanyl (1.5-2.0 µg/kg), anesthesia was initiated with propofol 2.5 mg/kg, desflurane/N2O 60% in O2 or desflurane/O2 alone. Anesthesia was maintained with either propofol 1.5-9.0 mg/kg/hr, desflurane 2.6-8.4% in N2O 60% in O2, or desflurane 3.1-8.9% in O2.

In 88 unpremedicated outpatients, anesthesia was initiated with thiopental 3-9 mg/kg or desflurane in O2. Anesthesia was maintained with isoflurane 0.7-1.4% in N2O 60%, desflurane 1.8-7.7% in N2O 60%, or desflurane 4.4-11.9% in O2.

Recovery from anesthesia was assessed at 30, 60, and 90 minutes following 0.5 MAC desflurane (3%) or isoflurane (0.6%) in N2O 60% using subjective and objective tests. At 30 minutes after anesthesia, only 43% of patients in the isoflurane group were able to perform the psychometric tests compared to 76% in the SUPRANE group (p < 0.05).

SUPRANE was studied in twelve volunteers receiving no other drugs. Hemodynamic effects during controlled ventilation (PaCO2 38 mm Hg) were:

*Differences were statistically significant (p < 0.05) compared to awake values, Newman-Keul’s method of multiple comparison.

When the same volunteers breathed spontaneously during desflurane anesthesia, systemic vascular resistance and mean arterial blood pressure decreased; cardiac index, heart rate, stroke volume, and central venous pressure (CVP) increased compared to values when the volunteers were conscious. Cardiac index, stroke volume, and CVP were greater during spontaneous ventilation than during controlled ventilation.

During spontaneous ventilation in the same volunteers, increasing the concentration of SUPRANE from 3% to 12% decreased tidal volume and increased arterial carbon dioxide tension and respiratory rate. The combination of N2O 60% with a given concentration of desflurane gave results similar to those with desflurane alone. Respiratory depression produced by desflurane is similar to that produced by other potent inhalation agents.

The use of desflurane concentrations higher than 1.5 MAC may produce apnea.

12.3 Pharmacokinetics
Due to the volatile nature of desflurane in plasma samples, the washin-washout profile of desflurane was used as a surrogate of plasma pharmacokinetics. SUPRANE is a volatile liquid inhalation anesthetic minimally biotransformed in the liver in humans. Less than 0.02% of the desflurane absorbed can be recovered as urinary metabolites (compared to 0.2% for isoflurane). Eight healthy male volunteers first breathed 70% N2O/30% O2 for 30 minutes and then a mixture of desflurane 2.0%, isoflurane 0.4%, and halothane 0.2% for another 30 minutes. During this time, inspired and end-tidal concentrations (FI and FA) were measured. The FA/FI (washin) value at 30 minutes for desflurane was 0.91, compared to 1.00 for N2O, 0.74 for isoflurane, and 0.58 for halothane (see Figure 2). The washin rates for halothane and isoflurane were similar to literature values. The washin was faster for desflurane than for isoflurane and halothane at all time points. The FA/FAO (washout) value at 5 minutes was 0.12 for desflurane, 0.22 for isoflurane, and 0.25 for halothane (see Figure 3). The washout for desflurane was more rapid than that for isoflurane and halothane at all elimination time points. By 5 days, the FA/FAO for desflurane is 1/20th of that for halothane or isoflurane.

12.5 Pharmacogenomics
RYR1 and CACNA1S are polymorphic genes and multiple pathogenic variants have been associated with malignant hyperthermia susceptibility (MHS) in patients receiving volatile anesthetic agents, including SUPRANE. Case reports as well as ex-vivo studies have identified multiple variants in RYR1 and CACNA1S associated with MHS. Variant pathogenicity should be assessed based on prior clinical experience, functional studies, prevalence information, or other evidence [see Contraindications (4), Warnings and Precautions (5.1)].

13. NONCLINICAL TOXICOLOGY

13.1 Carcinogenesis, Mutagenesis, Impairment of Fertility
Carcinogenesis: Long-term studies in animals to evaluate the carcinogenic potential of desflurane have not been conducted.

Mutagenesis: In vitro and in vivo genotoxicity studies did not demonstrate mutagenicity or chromosomal damage by desflurane. Tests for genotoxicity included the Ames mutation assay, the metaphase analysis of human lymphocytes, and the mouse micronucleus assay.

Impairment of Fertility: In a study in which male animals were administered 8.2% desflurane (60% oxygen) for either 0.5, 1.0, or 4.0 hours per day beginning 63 days prior to mating and female animals were administered the same doses of desflurane for 14 days prior to mating through Lactation Day 21, there were no adverse effects on fertility in the 1.0 hour per day treatment group. However, reduced male and female fertility was noted in the 4 hour a day group. A dose dependent increase in mortality and decreased body weight gain was note in all treatment groups.

13.2 Animal Toxicology and/or Pharmacology
Published studies in animals demonstrate that the use of anesthetic agents during the period of rapid brain growth or synaptogenesis results in widespread neuronal and oligodendrocyte cell loss in the developing brain and alterations in synaptic morphology and neurogenesis. Based on comparisons across species, the window of vulnerability to these changes is believed to correlate with exposures in the third trimester through the first several months of life, but may extend out to approximately 3 years of age in humans.

In primates, exposure to 3 hours of an anesthetic regimen that produced a light surgical plane of anesthesia did not increase neuronal cell loss, however, treatment regimens of 5 hours or longer increased neuronal cell loss. Data in rodents and in primates suggest that the neuronal and oligodendrocyte cell losses are associated with subtle but prolonged cognitive deficits in learning and memory. The clinical significance of these nonclinical findings is not known, and healthcare providers should balance the benefits of appropriate anesthesia in neonates and young children who require procedures against the potential risks suggested by the nonclinical data [See Warnings and Precautions (5.6) and Use in Specific Populations (8.1, 8.4)].

14. CLINICAL STUDIES

The efficacy of SUPRANE was evaluated in 1,843 patients including ambulatory (N=1,061), cardiovascular (N=277), geriatric (N=103), neurosurgical (N=40), and pediatric (N=235) patients. Clinical experience with these patients and with 1,087 control patients in these studies not receiving SUPRANE is described below. Although SUPRANE can be used in adults for the inhalation induction of anesthesia via mask, it produces a high incidence of respiratory irritation (coughing, breathholding, apnea, increased secretions, laryngospasm). Oxyhemoglobin saturation below 90% occurred in 6% of patients (from pooled data, N = 370 adults).

14.1 Ambulatory Surgery
SUPRANE plus N2O was compared to isoflurane plus N2O in multicenter studies (21 sites) of 792 ASA physical status I, II, or III patients aged 18-76 years (median 32).

Induction

Anesthetic induction begun with thiopental and continued with SUPRANE was associated with a 7% incidence of oxyhemoglobin saturation of 90% or less (from pooled data, N = 307) compared with 5% in patients in whom anesthesia was induced with thiopental and isoflurane (from pooled data, N = 152).

Maintenance & Recovery

SUPRANE with or without N2O or other anesthetics was generally well tolerated. There were no differences between SUPRANE and the other anesthetics studied in the times that patients were judged fit for discharge.

In one outpatient study, patients received a standardized anesthetic consisting of thiopental 4.2-4.4 mg/kg, fentanyl 3.5-4.0 µg/kg, vecuronium 0.05-0.07 mg/kg, and N2O 60% in oxygen with either desflurane 3% or isoflurane 0.6%. Emergence times were significantly different; but times to sit up and discharge were not different (see Table 5).

14.2 Cardiovascular Surgery
SUPRANE was compared to isoflurane, sufentanil or fentanyl for the anesthetic management of coronary artery bypass graft (CABG), abdominal aortic aneurysm, peripheral vascular and carotid endarterectomy surgery in 7 studies at 15 centers involving a total of 558 patients. In all patients except the desflurane vs. sufentanil study, the volatile anesthetics were supplemented with intravenous opioids, usually fentanyl. Blood pressure and heart rate were controlled by changes in concentration of the volatile anesthetics or opioids and cardiovascular drugs if necessary. Oxygen (100%) was the carrier gas in 253 of 277 desflurane cases (24 of 277 received N2O/O2).

No differences were found in cardiovascular outcome (death, myocardial infarction, ventricular tachycardia or fibrillation, heart failure) among desflurane and the other anesthetics.

Induction

SUPRANE should not be used as the sole agent for anesthetic induction in patients with coronary artery disease or any patients where increases in heart rate or blood pressure are undesirable. In the desflurane vs. sufentanil study, anesthetic induction with desflurane without opioids was associated with new transient ischemia in 14 patients vs. 0 in the sufentanil group. In the desflurane group, mean heart rate, arterial pressure, and pulmonary blood pressure increased and stroke volume decreased in contrast to no change in the sufentanil group. Cardiovascular drugs were used frequently in both groups: especially esmolol in the desflurane group (56% vs. 0%) and phenylephrine in the sufentanil group (43% vs. 27%). When 10 µg/kg of fentanyl was used to supplement induction of anesthesia at one other center, continuous 2-lead ECG analysis showed a low incidence of myocardial ischemia and no difference between desflurane and isoflurane. If desflurane is to be used in patients with coronary artery disease, it should be used in combination with other medications for induction of anesthesia, preferably intravenous opioids and hypnotics.

Maintenance & Recovery

In studies where SUPRANE or isoflurane anesthesia was supplemented with fentanyl, there were no differences in hemodynamic variables or the incidence of myocardial ischemia in the patients anesthetized with desflurane compared to those anesthetized with isoflurane.

During the precardiopulmonary bypass period, in the desflurane vs. sufentanil study where the desflurane patients received no intravenous opioid, more desflurane patients required cardiovascular adjuvants to control hemodynamics than the sufentanil patients. During this period, the incidence of ischemia detected by ECG or echocardiography was not statistically different between desflurane (18 of 99) and sufentanil (9 of 98) groups. However, the duration and severity of ECG-detected myocardial ischemia was significantly less in the desflurane group. The incidence of myocardial ischemia after cardiopulmonary bypass and in the ICU did not differ between groups.

14.3 Geriatric Surgery
SUPRANE plus N2O was compared to isoflurane plus N2O in a multicenter study (6 sites) of 203 ASA physical status II or III elderly patients, aged 57-91 years (median 71).

Induction

Most patients were premedicated with fentanyl (mean 2 µg/kg), preoxygenated, and received thiopental (mean 4.3 mg/kg IV) or thiamylal (mean 4 mg/kg IV) followed by succinylcholine (mean 1.4 mg/kg IV) for intubation.

Maintenance & Recovery

Heart rate and arterial blood pressure remained within 20% of preinduction baseline values during administration of SUPRANE 0.5-7.7% (average 3.6%) with 50-60% N2O. Induction, maintenance, and recovery cardiovascular measurements did not differ from those during isoflurane/N2O administration nor did the postoperative incidence of nausea and vomiting differ. The most common cardiovascular adverse event was hypotension occurring in 8% of the desflurane patients and 6% of the isoflurane patients.

14.4 Neurosurgery
SUPRANE was studied in 38 patients aged 26-76 years (median 48 years), ASA physical status II or III undergoing neurosurgical procedures for intracranial lesions.

Induction

Induction consisted of standard neuroanesthetic techniques including hyperventilation and thiopental.

Maintenance

No change in cerebrospinal fluid pressure (CSFP) was observed in 8 patients who had intracranial tumors when the dose of SUPRANE was 0.5 MAC in N2O 50%. In another study of 9 patients with intracranial tumors, 0.8 MAC desflurane/air/O2 did not increase CSFP above post induction baseline values. In a different study of 10 patients receiving 1.1 MAC desflurane/air/O2, CSFP increased 7 mm Hg (range 3-13 mm Hg increase, with final values of 11-26 mm Hg) above the pre-drug values.

All volatile anesthetics may increase intracranial pressure in patients with intracranial space occupying lesions. In such patients, SUPRANE should be administered at 0.8 MAC or less, and in conjunction with a barbiturate induction and hyperventilation (hypocapnia) in the period before cranial decompression. Appropriate attention must be paid to maintain cerebral perfusion pressure. The use of a lower dose of SUPRANE and the administration of a barbiturate and mannitol would be predicted to lessen the effect of desflurane on CSFP.

Under hypocapnic conditions (PaCO2 27 mm Hg) SUPRANE 1 and 1.5 MAC did not increase cerebral blood flow (CBF) in 9 patients undergoing craniotomies. CBF reactivity to increasing PaCO2 from 27 to 35 mm Hg was also maintained at 1.25 MAC desflurane/air/O2.

14.5 Pediatric Surgery
In a clinical safety trial conducted in children aged 2 to 16 years (mean 7.4 years), following induction with another agent, SUPRANE and isoflurane (in N2O/O2) were compared when delivered via face mask or laryngeal mask airway (LMA™ mask) for maintenance of anesthesia, after induction with intravenous propofol or inhaled sevoflurane, in order to assess the relative incidence of respiratory adverse events.

SUPRANE was associated with higher rates (compared with isoflurane) of coughing, laryngospasm and secretions with an overall rate of respiratory events of 39%. Of the pediatric patients exposed to desflurane, 5% experienced severe laryngospasm (associated with significant desaturation; i.e. SpO2 of <90% for >15 seconds, or requiring succinylcholine), across all ages, 2-16 years old. Individual age group incidences of severe laryngospasm were 9% for 2-6 years old, 1% for 7-11 years old, and 1% for 12-16 years old. Removal of LMA™ mask under deep anesthesia (MAC range 0.6 – 2.3 with a mean of 1.12 MAC) was associated with a further increase in frequency of respiratory adverse events as compared to awake LMA™ mask removal or LMA™ mask removal under deep anesthesia with the comparator. The frequency and severity of non-respiratory adverse events were comparable between the two groups.

The incidence of respiratory events under these conditions was highest in children aged 2-6 years. Therefore, similar studies in children under the age of 2 years were not initiated.

16. HOW SUPPLIED/STORAGE AND HANDLING

SUPRANE (desflurane, USP) is available in an amber-colored glass bottle or an aluminum bottle containing 240 mL of desflurane as follows:

Product repackaged by: Henry Schein, Inc., Bastian, VA 24314
From Original Manufacturer/Distributor's NDC and Unit of Sale | To Henry Schein Repackaged Product NDC and Unit of Sale | Total Strength/Total Volume (Concentration) per unit
NDC 10019-641-34 6 Units Aluminum Bottle | NDC 0404-9961-25 1 Aluminum Bottle in a bag (Bottle bears NDC 10019-641-64) | 240 mL

16.1 Safety and Handling
Occupational Caution

There is no specific work exposure limit established for SUPRANE. However, the National Institute for Occupational Safety and Health Administration (NIOSH) recommends that no worker should be exposed at ceiling concentrations greater than 2 ppm of any halogenated anesthetic agent over a sampling period not to exceed one hour.

Principle routes of exposure include:

Skin contact May cause skin irritation. In case of contact, immediately flush skin with plenty of water. Remove contaminated clothing and shoes. Seek medical attention if irritation develops.

Eye contact May cause eye irritation. In case of contact, immediately flush eyes with plenty of water for at least 15 minutes. Seek medical attention if irritation develops.

Ingestion No specific hazards other than therapeutic effects. Do NOT induce vomiting unless directed to do so by medical personnel. Never give anything by mouth to an unconscious person. If large quantities of this material are swallowed, seek medical attention immediately.

Inhalation If individuals smell vapors, or experience dizziness or headaches, they should be moved to an area with fresh air. Individuals could also experience the following: Cardiovascular effects: may include fluctuations in heart rate, changes in blood pressure, chest pain. Respiratory effects: may include shortness of breath, bronchospasms, laryngospasms, respiratory depression. Gastrointestinal effects: may include nausea, upset stomach, loss of appetite. Nervous System effects: may include ataxia, tremor, disturbance of speech, lethargy, headache, dizziness, blurred vision.

The predicted effects of acute overexposure by inhalation of SUPRANE include headache, dizziness or (in extreme cases) unconsciousness [See Overdosage (10)].

There are no documented adverse effects of chronic exposure to halogenated anesthetic vapors (Waste Anesthetic Gases or WAGs) in the workplace. Although results of some epidemiological studies suggest a link between exposure to halogenated anesthetics and increased health problems (particularly spontaneous abortion), the relationship is not conclusive. Since exposure to WAGs is one possible factor in the findings for these studies, operating room personnel, and pregnant women in particular, should minimize exposure. Precautions include adequate general ventilation in the operating room, the use of a well-designed and well-maintained scavenging system; work practices to minimize leaks and spills while the anesthetic agent is in use, and routine equipment maintenance to minimize leaks.

Consistent with clinical data, concentrations would need to reach 2-3% in inspired air before individuals would likely experience dizziness or other physiologic effects.

16.2 Storage
Store at room temperature, 15°-30°C (59°-86°F). SUPRANE has been demonstrated to be stable for the period defined by the expiration dating on the label. The bottle should be recapped after each use of SUPRANE.

17. PATIENT COUNSELING INFORMATION

Anesthesia providers need to obtain the following information from patients prior to administration of anesthesia:

• Medications they are taking, including herbal supplements
• Drug allergies, including allergic reactions to anesthetic agents (including hepatic sensitivity)
• Any history of severe reactions to prior administration of anesthetic
• If the patient or a member of the patient’s family has a history of malignant hyperthermia or if the patient has a history of Duchenne muscular dystrophy or other latent neuromuscular disease
Anesthesia providers should inform patients of the risks associated with SUPRANE:

• Post-operative nausea and vomiting and respiratory adverse effects including coughing.
• There is no information of the effects of SUPRANE following anesthesia on the ability to operate an automobile or other heavy machinery. However, patients should be advised that the ability to perform such tasks may be impaired after receiving anesthetic agents.
Anesthesia providers should inform parents and caregivers of pediatric patients that emergence from anesthesia in children may evoke a brief state of agitation that may hinder cooperation.

Effect of anesthetic and sedation drugs on early brain development

Studies conducted in young animals and children suggest repeated or prolonged use of general anesthetic or sedation drugs in children younger than 3 years may have negative effects on their developing brains. Discuss with parents and caregivers the benefits, risks, and timing and duration of surgery or procedures requiring anesthetic and sedation drugs [See Warnings and Precautions (5.6)].

************************************************************************

Baxter and Suprane are registered trademarks of Baxter International Inc.

LMA is a trademark of The Laryngeal Mask Company Limited and is used under license.

Manufactured for
Baxter Healthcare Corporation
Deerfield, IL 60015 USA

************************************************************************

07-19-00-5887